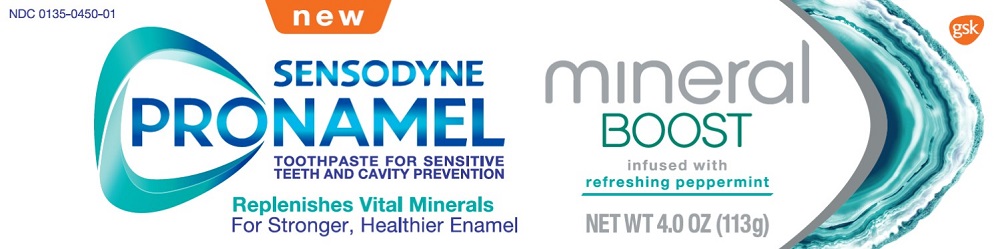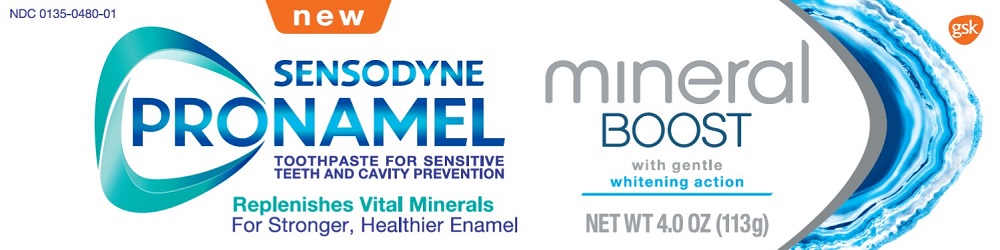 DRUG LABEL: SENSODYNE PRONAMEL
NDC: 0135-0450 | Form: PASTE
Manufacturer: Haleon US Holdings LLC
Category: otc | Type: HUMAN OTC DRUG LABEL
Date: 20240304

ACTIVE INGREDIENTS: POTASSIUM NITRATE 50 mg/1 g; SODIUM FLUORIDE 1.15 mg/1 g
INACTIVE INGREDIENTS: WATER; SORBITOL; HYDRATED SILICA; GLYCERIN; COCAMIDOPROPYL BETAINE; XANTHAN GUM; TITANIUM DIOXIDE; SACCHARIN SODIUM

Drug Facts

Active ingredient

Potassium nitrate 5%

Sodium fluoride 0.25% (0.15% w/v fluoride ion)

Purpose

Antihypersensitivity

Anticavity

Uses

- builds increasing protection against painful sensitivity of the teeth to cold, heat, acids, sweets, or contact.
- aids in the prevention of dental cavities.

Warnings

Stop use and ask a dentist if

- the problem persists or worsens. Sensitive teeth may indicate a serious problem that may need prompt care by a dentist.
- pain/sensitivity still persists after 4 weeks of use.

Keep out of reach of children.

If more than used for brushing is accidentally swallowed, get medical help or contact a Poison Control Center right away.

Directions

- adults and children 12 years of age and older:
  - apply at least a 1-inch strip of the product onto a soft bristle toothbrush.
  - brush teeth thoroughly for at least 1 minute twice a day (morning and evening), and not more than 3 times a day, or as recommended by a dentist or doctor. Make sure to brush all sensitive areas of the teeth. Minimize swallowing. Spit out after brushing
- children under 12 years of age:Consult a dentist or doctor.

Other information

- do not store above 25°C (77°F)

Inactive ingredients (refreshing peppermint)

water, sorbitol, hydrated silica, glycerin, flavor, cocamidopropyl betaine, xanthan gum, titanium dioxide, sodium saccharin

Inactive ingredients (whitening action)

water, sorbitol, hydrated silica, glycerin, cocamidopropyl betaine, flavor, xanthan gum, titanium dioxide, sodium saccharin, sodium hydroxide

Questions or comments?

1-866-844-2797

Additional Information

Does not contain: SLS/sulfates • artificial dyes • parabens • triclosan • peroxide

Minerals keep enamel strong and white. But acidic foods & drinks can dissolve surface minerals. Your saliva naturally replenishes minerals but can’t always keep up, leading to enamel loss.

Pronamel Mineral Boost improves natural mineral absorption for strong white teeth, protected from sensitivity.

ACIDS DISSOLVE SURFACE MINERALS…

…PRONAMEL BOOSTS MINERAL ABSORPTION FROM SALIVA

Replenishes vital minerals in enamel.

Developed to maximize the effect of fluoride to boost the absorption of calcium & phosphate into the enamel surface.

With twice-daily brushing, Pronamel helps to:

- Protect against effects of dietary acids
- Prevent enamel loss
- Relieve sensitive teeth
- Protect against cavities
- Clean and freshen your mouth

Recyclable Carton

Save Water

Turn off tap while brushing

Trademarks are owned by or licensed to the GSK group of companies.

Distributed by:

GSK Consumer Healthcare

Warren, NJ 07059

Principal Display Panel

NDC 0135-0450-01

SENSODYNE

PRONAMEL

MINERAL BOOST

new

TOOTHPASTE FOR SENSITIVE TEETH AND CAVITY PREVENTION

Replenishes Vital Minerals

For Stronger, Healthier Enamel

infused with refreshing peppermint

NET WT 4.0 OZ (113g)

gsk

©2020 GSK group of companies or its licensor.

62000000049368

Principal Display Panel

NDC 0135-0480-01

SENSODYNE

PRONAMEL

MINERAL BOOST

new

TOOTHPASTE FOR SENSITIVE TEETH AND CAVITY PREVENTION

Replenishes Vital Minerals

For Stronger, Healthier Enamel

With gentle whitening action

NET WT 4.0 OZ (113g)

gsk

©2020 GSK group of companies or its licensor.

62000000049369